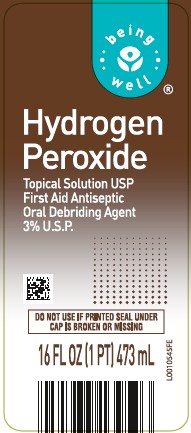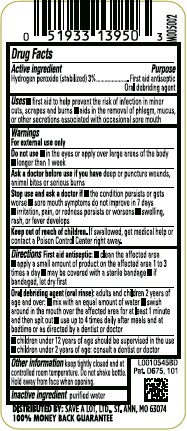 DRUG LABEL: Hydrogen Peroxide
NDC: 46994-871 | Form: SOLUTION
Manufacturer: Save-A-Lot Food Stores Ltd
Category: otc | Type: HUMAN OTC DRUG LABEL
Date: 20260219

ACTIVE INGREDIENTS: HYDROGEN PEROXIDE 30 mg/1 mL
INACTIVE INGREDIENTS: WATER

Being Well 871.000/871AA
Hydrogen Peroxide 3%

Active ingredient

Hydrogen peroxide (stabilized) 3%

Purpose

First Aid Antiseptic

Oral Debriding agent

Uses

- first aid to help prevent the risk of infection in minor cuts, scrapes and burns
- aids in the removal of phlegm, mucus, or the other secretions associated with occasional sore mouth

Warnings

For external use only

Do not use

- in the eyes or apply over large areas of the body
- longer than 1 week

Ask a doctor before use if you have

deep or puncture wounds, animal bites or serious burns

Stop use and ask a doctor if

- the condition persists or gets worse
- sore mouth symptoms do not improve in 7 days
- irritation, pain, or redness persists or worsens
- swelling, rash, or fever develops

Keep out of reach of children.

If swallowed, get medical help or contact a Poison Control Center right away.

Directions

First aid antiseptic:

- clean the affected area
- apply a small amound of product on the affected area 1 to 3 times a day
- may be covered with a sterile bandage
- if bandaged, let dry first

Oral debriding agent: adults, children over 2 years of age:

- mix with equal amount of water
- swish around in the mouth over the affected area for at least 1 minute, then spit out
- use up to 4 times daily after meals and at bedtime

- children under 12 years of age should be supervised in the use.
- children under 2 years of age: consult a dentist, doctor

Other information

Keep tightly closed and at controlled room temperature. Do not shake bottle. Hold away from face when opening.

Inactive ingredient

purified water

ADVERSE REACTION

DISTRIBUTED BY: SAVE A LOT, LTD., ST. ANN, MO 63074

100% MONEY BACK GUARANTEE

Pat. D675, 101

Principal display panel

Being Well®

Hydrogen Peroxide

TOPICAL SOLUTION USP

First Aid Antiseptic

Oral Debriding Agent

3% U.S.P.

Do not use if printed seal under cap is broken or missing

16 FL OZ (1 PT) 473 mL